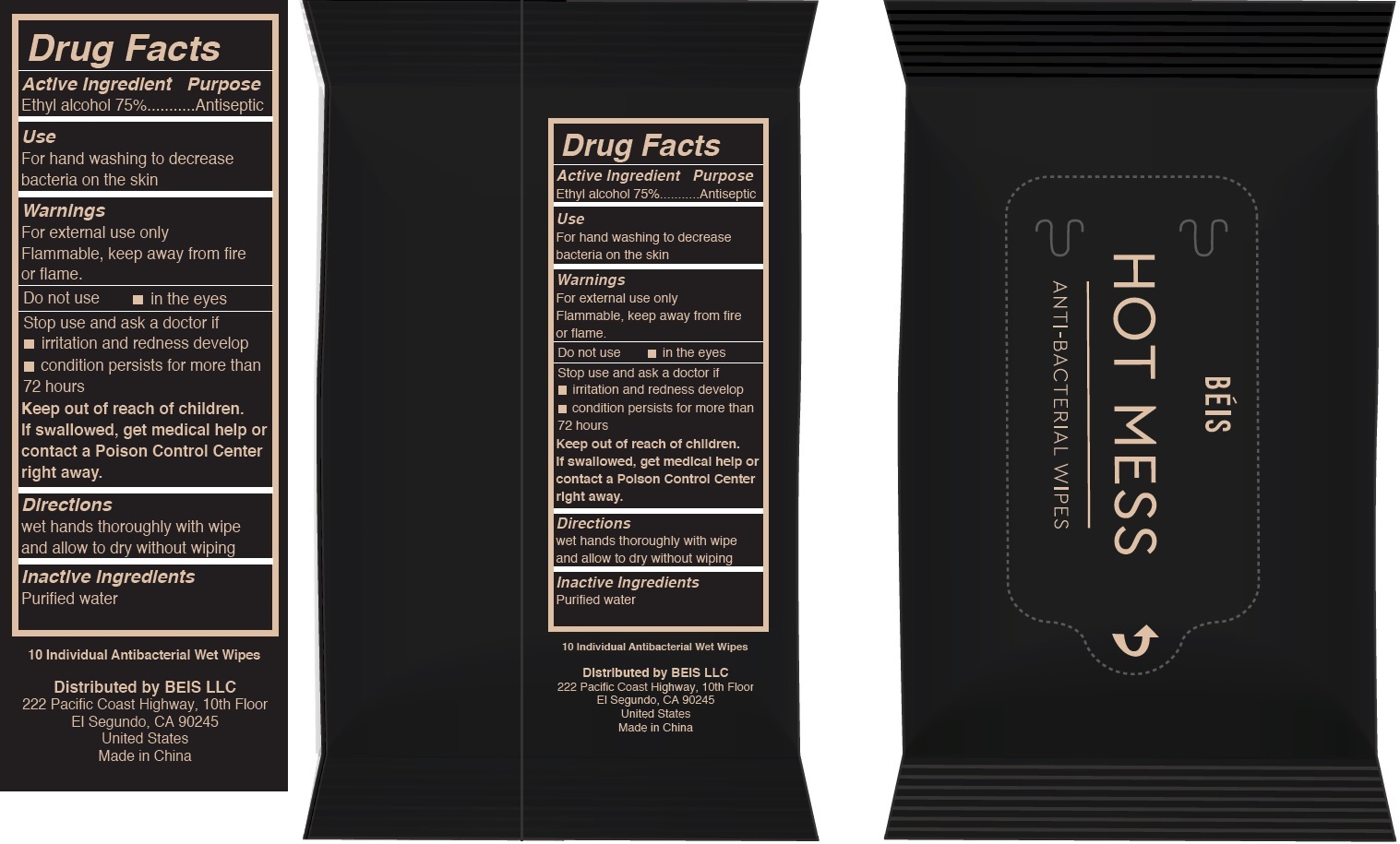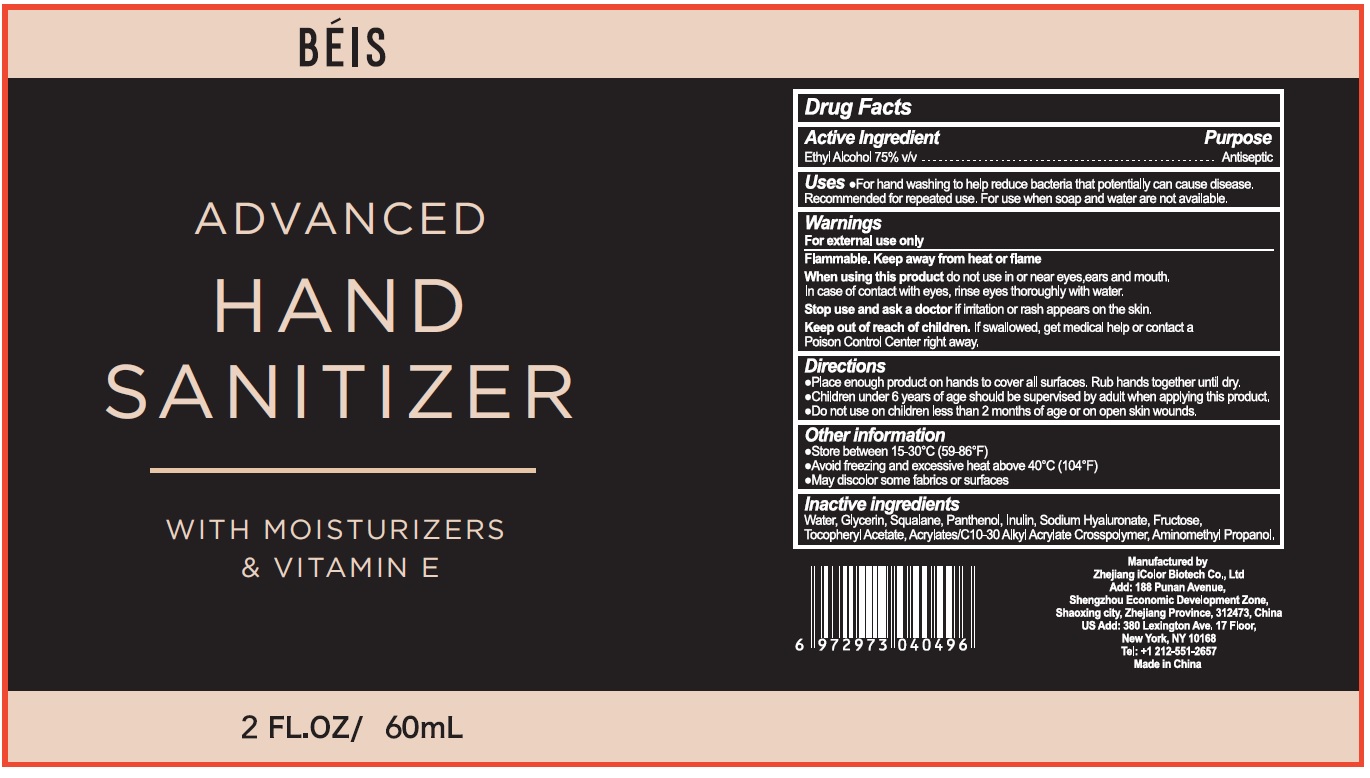 DRUG LABEL: BEIS Clean Kit
NDC: 81263-003 | Form: KIT | Route: TOPICAL
Manufacturer: Beis LLC
Category: otc | Type: HUMAN OTC DRUG LABEL
Date: 20211123

ACTIVE INGREDIENTS: ALCOHOL 75 mL/100 mL; ALCOHOL 75 mL/100 mL
INACTIVE INGREDIENTS: WATER; GLYCERIN; SQUALANE; PANTHENOL; INULIN; HYALURONATE SODIUM; FRUCTOSE; .ALPHA.-TOCOPHEROL ACETATE; CARBOMER INTERPOLYMER TYPE A (ALLYL SUCROSE CROSSLINKED); AMINOMETHYLPROPANOL; WATER

BEIS Clean Kit

Active Ingredient

Ethyl Alcohol 75% v/v

Purpose

Antiseptic

Uses

- For hand washing to help reduce bacteria that potentially can cuase disease. Recommended for repeated use. For use when soap and water are not available.

Warnings

For external use only

Flammable, Keep away from heat or flame

When using this product

do not use in or near eyes,ears and mouth, In case of contact with eyes, rinse eyes thoroughly with water.

Stop use and ask a doctor

if irritation or rash appears on the skin.

Keep out of reach of children.

If swallowed, get medical help or contact a Poison Control Center right away.

Directions

- Place enough product on hands to cover all surfaces. Rub hands together until dry.
- Children under 6 years of age should be supervised by adult when applying this product.
- Do not use on children less than 2 months of age or on open skin wounds.

Other information

- Store between 15-30°C (59-86°F)
- Avoid freezing and excessive heat above 40°C (104°F)
- May discolor some fabrics or surfaces

Inactive ingredients

Water, Glycerin, Squalane, Panthenol, Inulin, Sodium Hyaluronate, Fructose, Tocopheryl Acetate, Acrylates/C10-30 Alkyl Acrylate Crosspolymer, Aminomethyl Propanol.

Active Ingredient

Ethyl alcohol 75%

Purpose

Antiseptic

Use

For hand washing to decrease bacteria on the skin

Warnings

For external use only

Flammable, keep away from fire or flame.

Do not use

- in the eyes

Stop use and ask a doctor if

- irritation and redness develop
- condition persists for more than 72 hours

Keep out of reach of children.

If swallowed, get medical help or contact a Poison Control Center right away.

Directions

wet hands thoroughly with wipe and allow to dry without wiping

Inactive Ingredients

Purified water